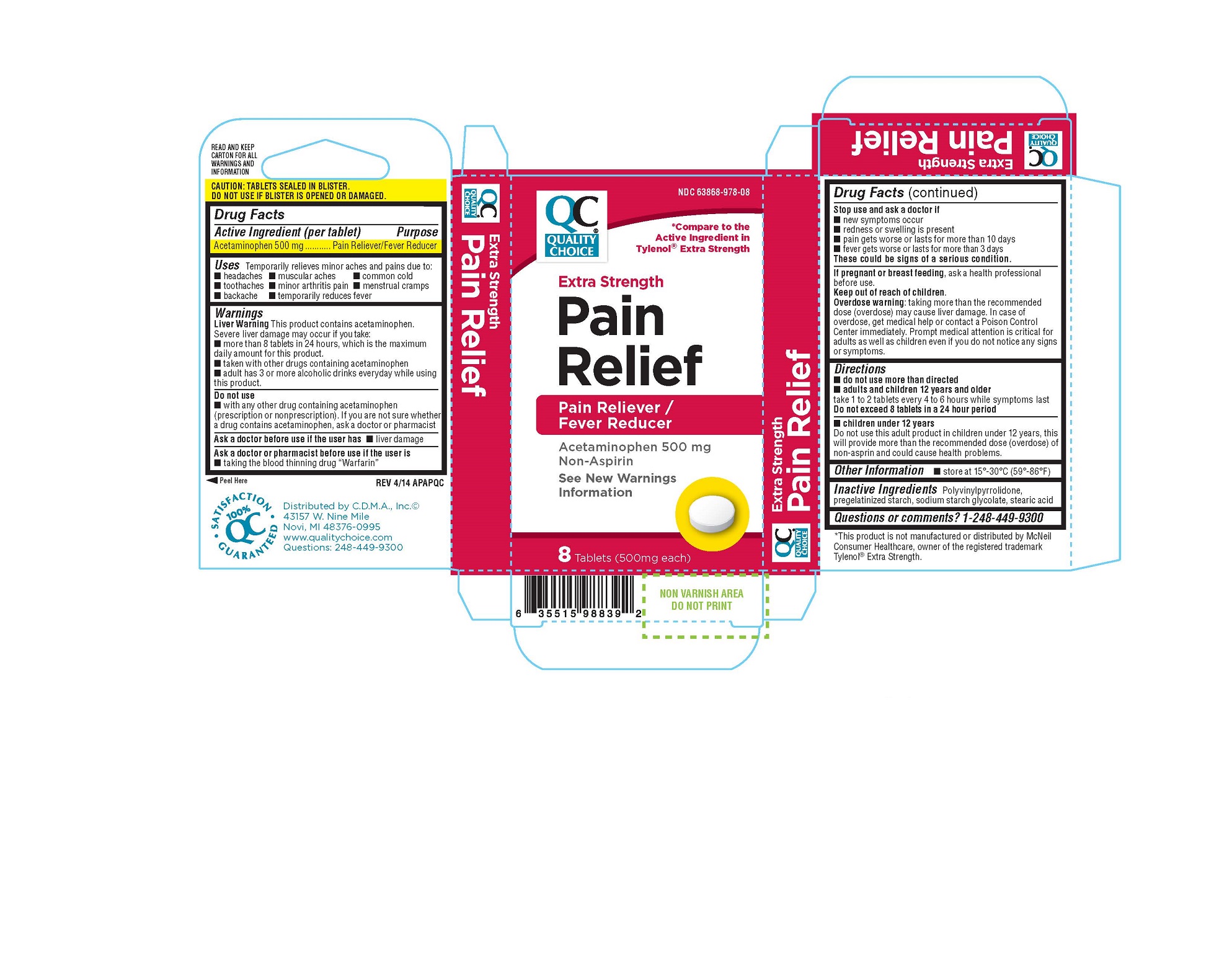 DRUG LABEL: Quality Choice Extra Strength Pain Relief
NDC: 63868-978 | Form: TABLET
Manufacturer: Chain Drug Marketing Association
Category: otc | Type: HUMAN OTC DRUG LABEL
Date: 20140823

ACTIVE INGREDIENTS: ACETAMINOPHEN 500 mg/1 1
INACTIVE INGREDIENTS: POVIDONE K30;  SODIUM STARCH GLYCOLATE TYPE A POTATO ; STEARIC ACID

DRUG FACTS

Active ingredient

Acetaminophen

Purpose

Pain reliever/fever reducer

Uses

- temporarily relieves minor aches and pains due to:
  - headache
  - backache
  - toothache
  - the common cold
  - minor pain of arthritis
  - muscular aches
  - premenstrual and menstrual cramps
- temporarily reduces fever

Warnings

Liver warning: This product contains acetaminophen. The maximum daily dosse of this product is 6 caplets (3,000 mg) in 24 hours. Severe liver damage may occur if you take:

- more than 4,000 mg of acetaminophen in 24 hours
- with other drugs containing acetaminophen
- 3 or more alcoholic drinks every day while using this product

Ask a doctor before use if you have
liver disease.
Ask a doctor or pharmacist before use if you are
taking the blood thinning drug warfarin.

Stop use and ask a doctor if

- pain gets worse or lasts more than 10 days
- fever gets worse or lasts more than 3 days
- new symptoms occur
- redness or swelling is present

These could be signs of a serious condition.

PREGNANCY OR BREAST FEEDING

If pregnant or breast-feeding, ask a health professional before use.

Keep out of reach of children
Overdose warning: Taking more than the recommended dose (overdose) may cause liver damamge. In case of overdose, get medical help or contact a Poison Control Center (1-800-222-1222) right away. Quick medical attention is critical for adults as well as for children even if you do not notice any signs or symptoms.

Directions

- do not take more than directed (see overdose warning)
- adults and children 12 years and over
  - take 2 caplets every 4 to 6 hours while symptoms last
  - do not take more than 8 caplets in 24 hours
  - do not take for more than 10 days unless directed by a doctor
- children under 12 years: do not use this adult extra strength product in children under 12 years of age; this will provide more than the recommended dose (overdose) of acetaminophen and may cause liver damage

Other Information

- store 25ºC (77ºF); excursions permitted between 15°-30°C (59°-86°F)
- see end flap for expiration date and lot number

Inactive Ingredients
Polyvinylpyrrolidone, pregelatinized starch, sodium starch glycolate, stearic acid